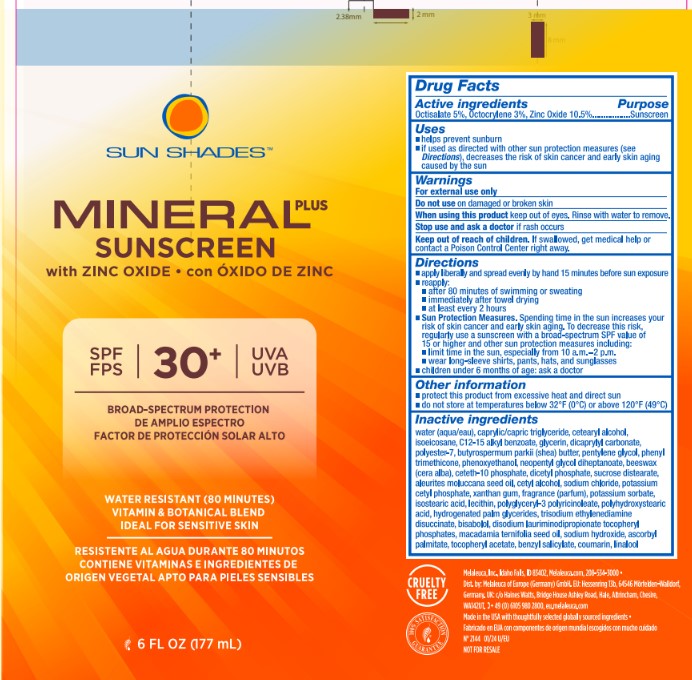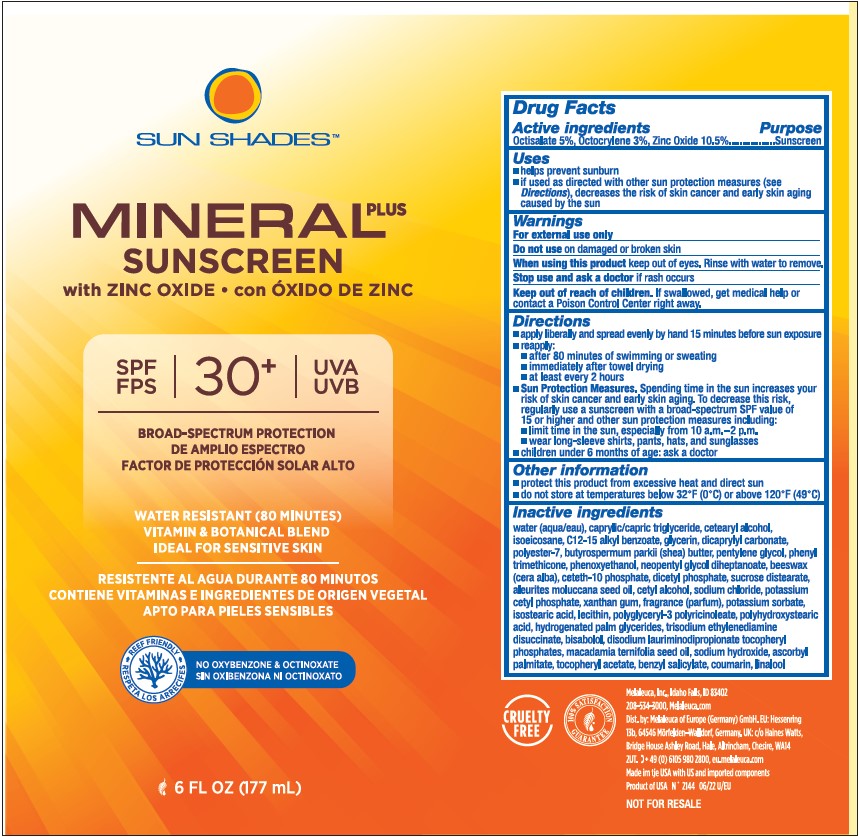 DRUG LABEL: Sun Shades Mineral Plus Sunscreen
NDC: 54473-218 | Form: LOTION
Manufacturer: Melaleuca Inc.
Category: otc | Type: HUMAN OTC DRUG LABEL
Date: 20251231

ACTIVE INGREDIENTS: OCTISALATE 9.225 g/177 mL; OCTOCRYLENE 5.535 g/177 mL; ZINC OXIDE 18.45 g/177 mL
INACTIVE INGREDIENTS: NEOPENTYL GLYCOL DIHEPTANOATE; PENTYLENE GLYCOL; PHENOXYETHANOL; PHENYL TRIMETHICONE; POTASSIUM CETYL PHOSPHATE; POTASSIUM SORBATE; SHEANUT OIL; SODIUM CHLORIDE; SUCROSE DISTEARATE; .ALPHA.-TOCOPHEROL ACETATE; WATER; XANTHAN GUM; YELLOW WAX; SODIUM HYDROXIDE; ALKYL (C12-15) BENZOATE; ASCORBYL PALMITATE; CETETH-10 PHOSPHATE; CETOSTEARYL ALCOHOL; CETYL ALCOHOL; DICAPRYLYL CARBONATE; DIHEXADECYL PHOSPHATE; DISODIUM LAURIMINODIPROPIONATE TOCOPHERYL PHOSPHATES; GLYCERIN; HYDROGENATED PALM GLYCERIDES; ISOEICOSANE; ISOSTEARIC ACID; KUKUI NUT OIL; LEVOMENOL; MACADAMIA OIL; MEDIUM-CHAIN TRIGLYCERIDES; TRISODIUM ETHYLENEDIAMINE DISUCCINATE

Sun Shades Mineral Plus SPF 30+ Sunscreen

Active ingredients

Octisalate 5%, Octocrylene 3%, Zinc Oxide 10.5%

Purpose

Sunscreen

Uses

■ helps prevent sunburn

■ if used as directed with other sun protection measures (see Directions), decreases the risk of skin cancer and early skin aging caused by the sun

Warnings

For external use only

Do not use on damaged or broken skin

When using this product keep out of eyes. Rinse with water to remove.

Stop use and ask a doctor if rash occurs

Keep out of reach of children. If swallowed, get medical help or contact a Poison Control Center right away.

Directions

■ apply liberally and spread evenly by hand 15 minutes before sun exposure

■ reapply:

■ after 80 minutes of swimming or sweating

■ immediately after towel drying

■ at least every 2 hours

■ Sun Protection Measures. Spending time in the sun increases your risk of skin cancer and early signs of aging. To decrease this risk, regularly use a sunscreen with a broad-spectrum SPF value of 15 or higher and other sun protection measures including:

■ limit time in the sun, especially from 10 AM-2 PM

■ wear long-sleeve shirts, pants, hats, and sunglasses

■ children under 6 months of age: ask a doctor

Other information

■ protect this product from excessive heat and direct sun

■ do not store at temperatures below 32°F (0°C) or above 120°F (49°C)

Inactive ingredients

water (aqua/eau), caprylic/capric triglyceride, cetearyl alcohol, isoeicosane, C12-15 alkyl benzoate, glycerin, dicaprylyl carbonate, polyester-7, butyrospermum parkii (shea) butter, pentylene glycol, phenyl trimethicone, phenoxyethanol, neopentyl glycol diheptanoate, beeswax (cera alba), ceteth-10 phosphate, dicetyl phosphate, sucrose distearate, aleurites moluccana seed oil, cetyl alcohol, sodium chloride, potassium cetyl phosphate, xanthan gum, fragrance (parfum), potassium sorbate, isostearic acid, lecithin, polyglyceryl-3 polyricinoleate, polyhydroxystearic acid, hydrogenated palm glycerides, trisodium ethylenediamine disuccinate, bisabolol, disodium lauriminodipropionate tocopheryl phosphates, macadamia ternifolia seed oil, sodium hydroxide, ascorbyl palmitate, tocopheryl acetate, benzyl salicylate, coumarin, linalool